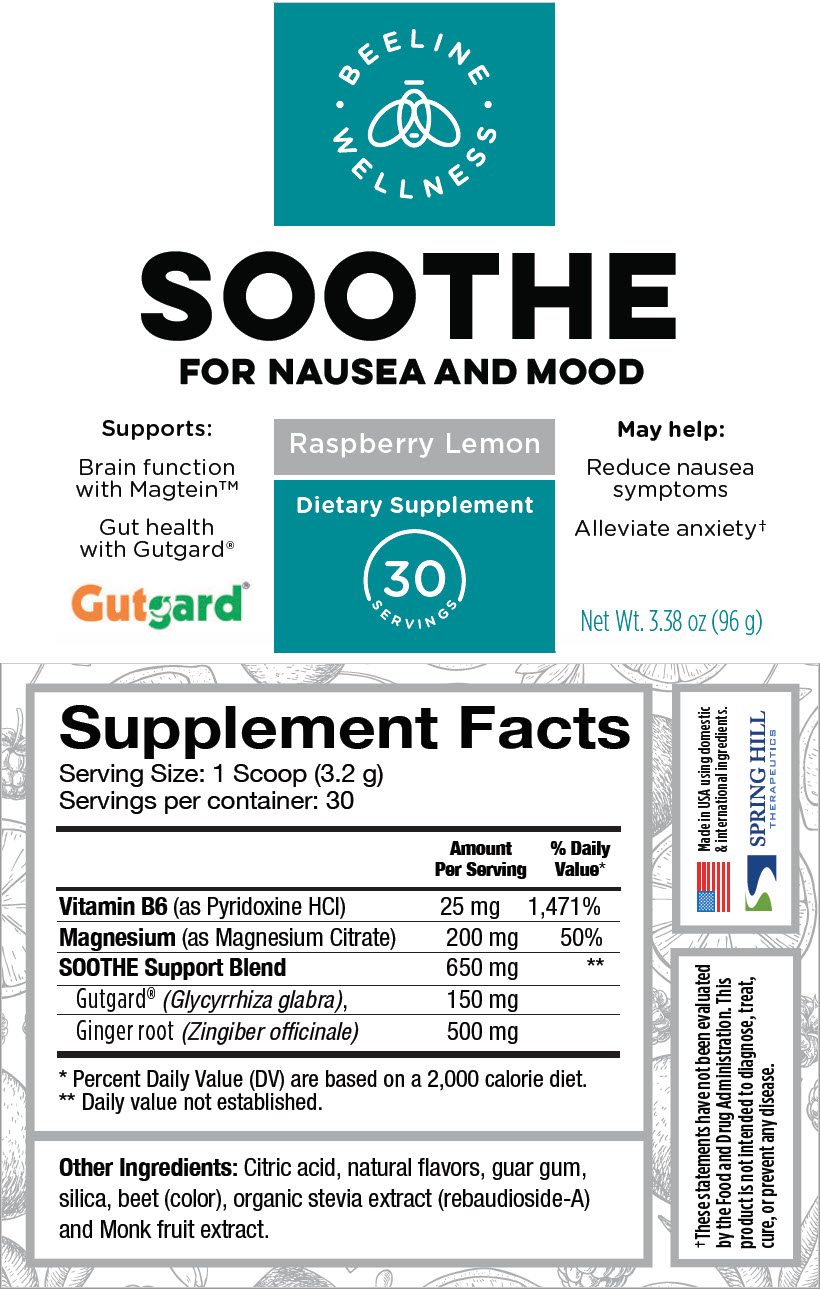 DRUG LABEL: Soothe
NDC: 69833-050 | Form: POWDER, FOR SOLUTION
Manufacturer: Spring Hill Therapeutics LLC
Category: other | Type: DIETARY SUPPLEMENT
Date: 20200901

ACTIVE INGREDIENTS: PYRIDOXINE HYDROCHLORIDE 25 mg/3.2 g; MAGNESIUM CITRATE 200 mg/3.2 g; GLYCYRRHIZA GLABRA 150 mg/3.2 g; GINGER 500 mg/3.2 g
INACTIVE INGREDIENTS: CITRIC ACID MONOHYDRATE; GUAR GUM; SILICON DIOXIDE; REBAUDIOSIDE A

SOOTHE

STATEMENT OF IDENTITY

Supplement Facts
Serving Size: 1 Scoop (3.2 g)
Servings per container: 30
 | Amount Per Serving | % Daily Value [Percent Daily Value (DV) are based on a 2,000 calorie diet.]
Vitamin B6 (as Pyridoxine HCl) | 25 mg | 1,471%
Magnesium (as Magnesium Citrate) | 200 mg | 50%
SOOTHE Support Blend | 650 mg | [Daily value not established.]
Gutgard® (Glycyrrhiza glabra), | 150 mg
Ginger root (Zingiber officinale) | 500 mg

Other Ingredients: Citric acid, natural flavors, guar gum, silica, beet (color), organic stevia extract (rebaudioside-A) and Monk fruit extract.

HEALTH CLAIM

†These statements have not been evaluated by the Food and Drug Administration. This product is not intended to diagnose, treat, cure, or prevent any disease.

Made in USA using domestic & international ingredients.

SPRING HILL
THERAPEUTICS

PRINCIPAL DISPLAY PANEL - 96 g Canister Label

BEELINE
WELLNESS

SOOTHE
FOR NAUSEA AND MOOD

Supports:

Brain function
with Magtein™

Gut health
with Gutgard®

Gutgard®

Raspberry Lemon

Dietary Supplement

30
SERVINGS

May help:

Reduce nausea
symptoms

Alleviate anxiety†

Net Wt. 3.38 oz (96 g)